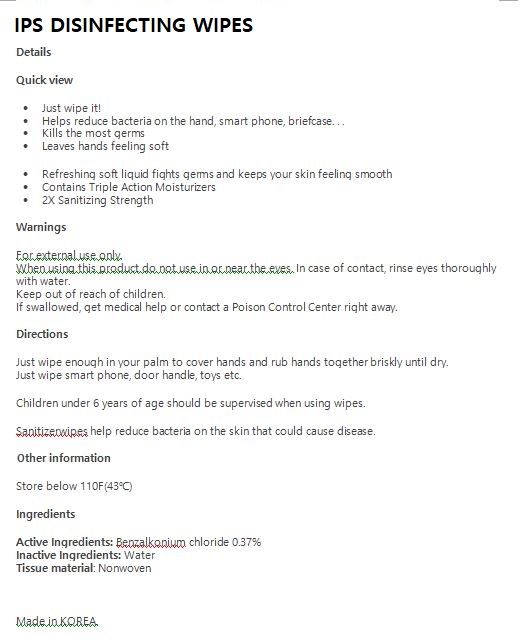 DRUG LABEL: IPS DISINFECTING WIPES
NDC: 74085-0008 | Form: LIQUID
Manufacturer: BIOCHEM KOREA CO LTD
Category: otc | Type: HUMAN OTC DRUG LABEL
Date: 20201224

ACTIVE INGREDIENTS: BENZALKONIUM CHLORIDE 0.37 g/100 g
INACTIVE INGREDIENTS: WATER

Drug Facts

ACTIVE INGREDIENT

Benzalkonium chloride 0.37%

PURPOSE

first aid to help prevent the risk of infection in minor cuts, scrapes, and burns.

KEEP OUT OF REACH OF THE CHILDREN

INDICATIONS AND USAGE

Clean affected area

Apply small amount of this product on the area 1-3 times daily

If bandaged, let dry first

May be covered with a sterile bandage

WARNINGS

■ For external use only.

■ Do not use in eyes.

■ lf swallowed, get medical help promptly.

■ Stop use, ask doctor lf irritation occurs.

■ Keep out of reach of children.

DOSAGE AND ADMINISTRATION

for external use only

INACTIVE INGREDIENT

Water